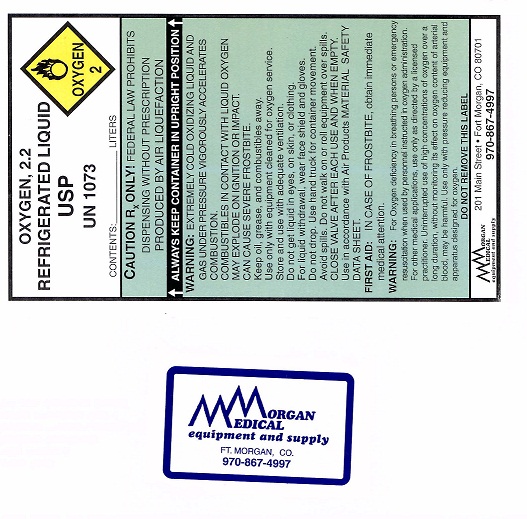 DRUG LABEL: Oxygen
NDC: 52084-0001 | Form: GAS
Manufacturer: Morgan Medical Equipment & Supply
Category: prescription | Type: HUMAN PRESCRIPTION DRUG LABEL
Date: 20100315

ACTIVE INGREDIENTS: Oxygen 99 L/100 L

Oxygen